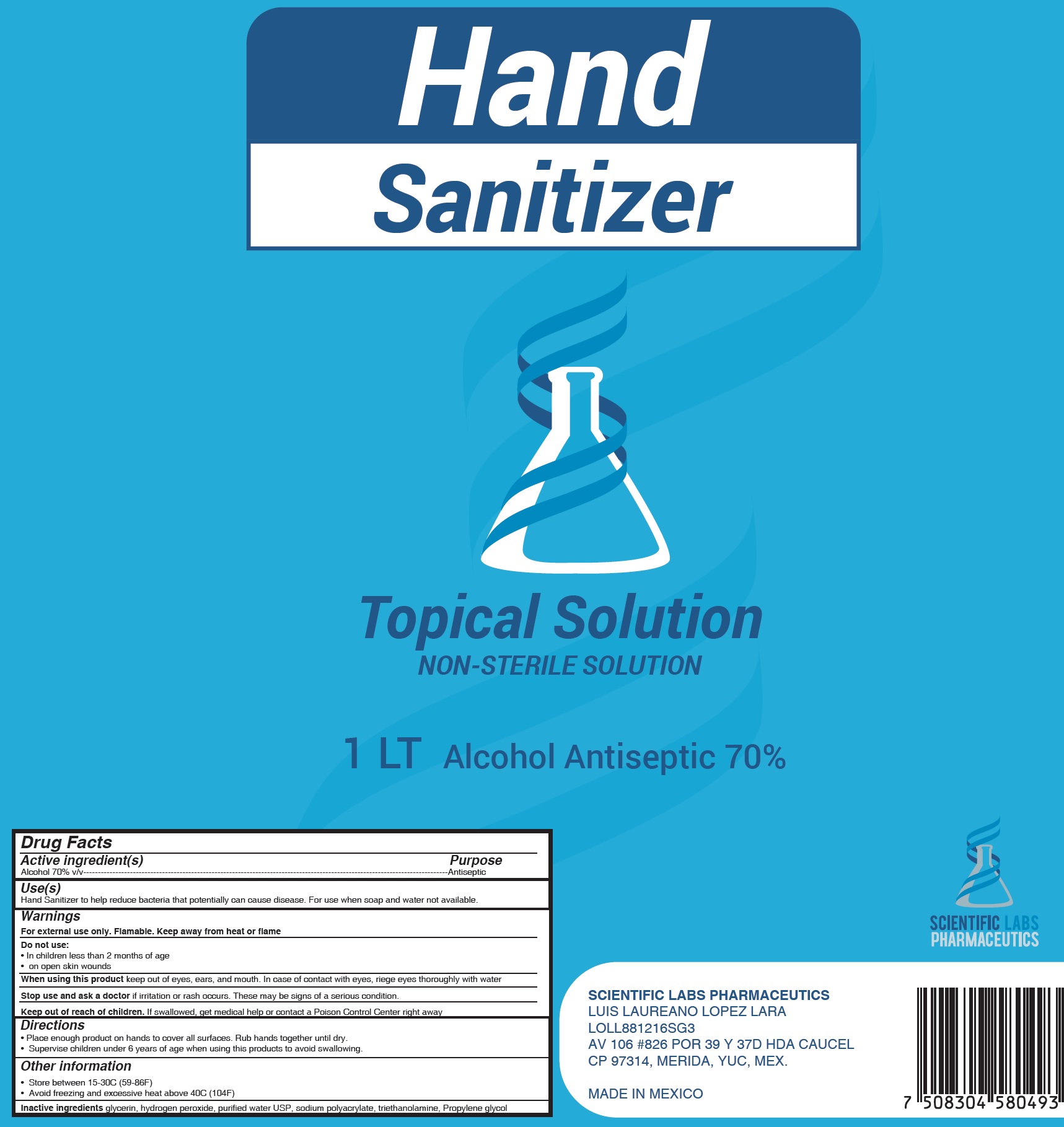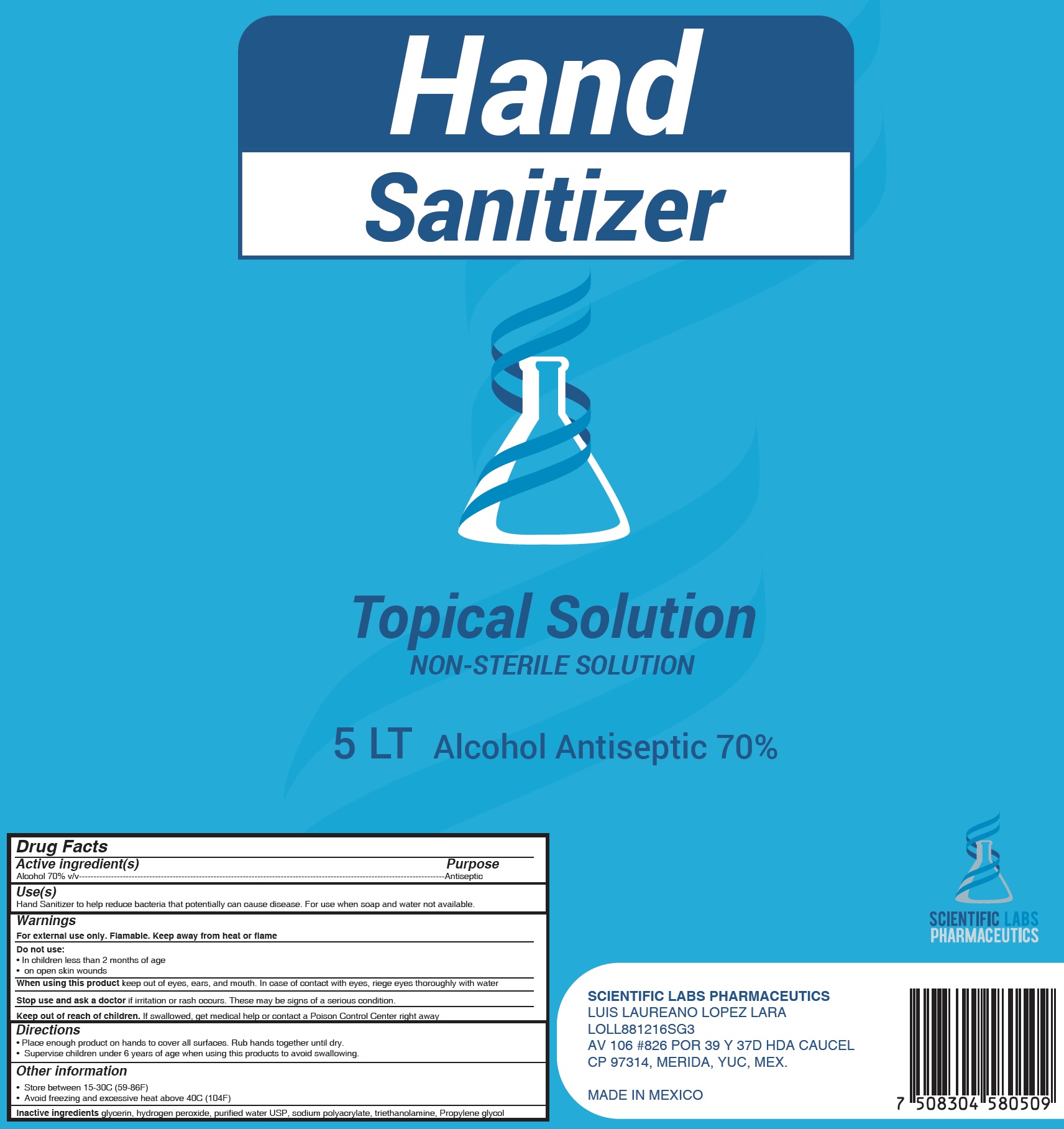 DRUG LABEL: Hand Sanitizer
NDC: 79796-000 | Form: GEL
Manufacturer: Scientific Labs
Category: otc | Type: HUMAN OTC DRUG LABEL
Date: 20200803

ACTIVE INGREDIENTS: ALCOHOL 0.7 mL/1 mL
INACTIVE INGREDIENTS: GLYCERIN; HYDROGEN PEROXIDE; WATER; TROLAMINE; PROPYLENE GLYCOL

Hand Sanitizer Topical Solution

Active ingredient(s)

Alcohol 70% v/v

Purpose

Antiseptic

Use(s)

Hand Sanitizer to help reduce bacteria that potentially can cause disease. For use when soap and water not available.

Warnings

For external use only. Flamable. Keep away from heat or flame

Do not use:

• In children less than 2 months of age
• on open skin wounds

When using this product

keep out of eyes, ears, and mouth. In case of contact with eyes, riege eyes thoroughly with water

Stop use and ask a doctor

if irritation or rash occurs. These may be signs of a serious condition.

Keep out of reach of children.

If swallowed, get medical help or contact a Poison Control Center right away

Directions

• Place enough product on hands to cover all surfaces. Rub hands together until dry.
• Supervise children under 6 years of age when using this products to avoid swallowing.

Other information

• Store between 15-30C (59-86F)
• Avoid freezing and excessive heat above 40C (104F)

Inactive ingredients

glycerin, hydrogen peroxide, purified water USP, sodium polyacrylate, triethanolamine, Propylene glycol